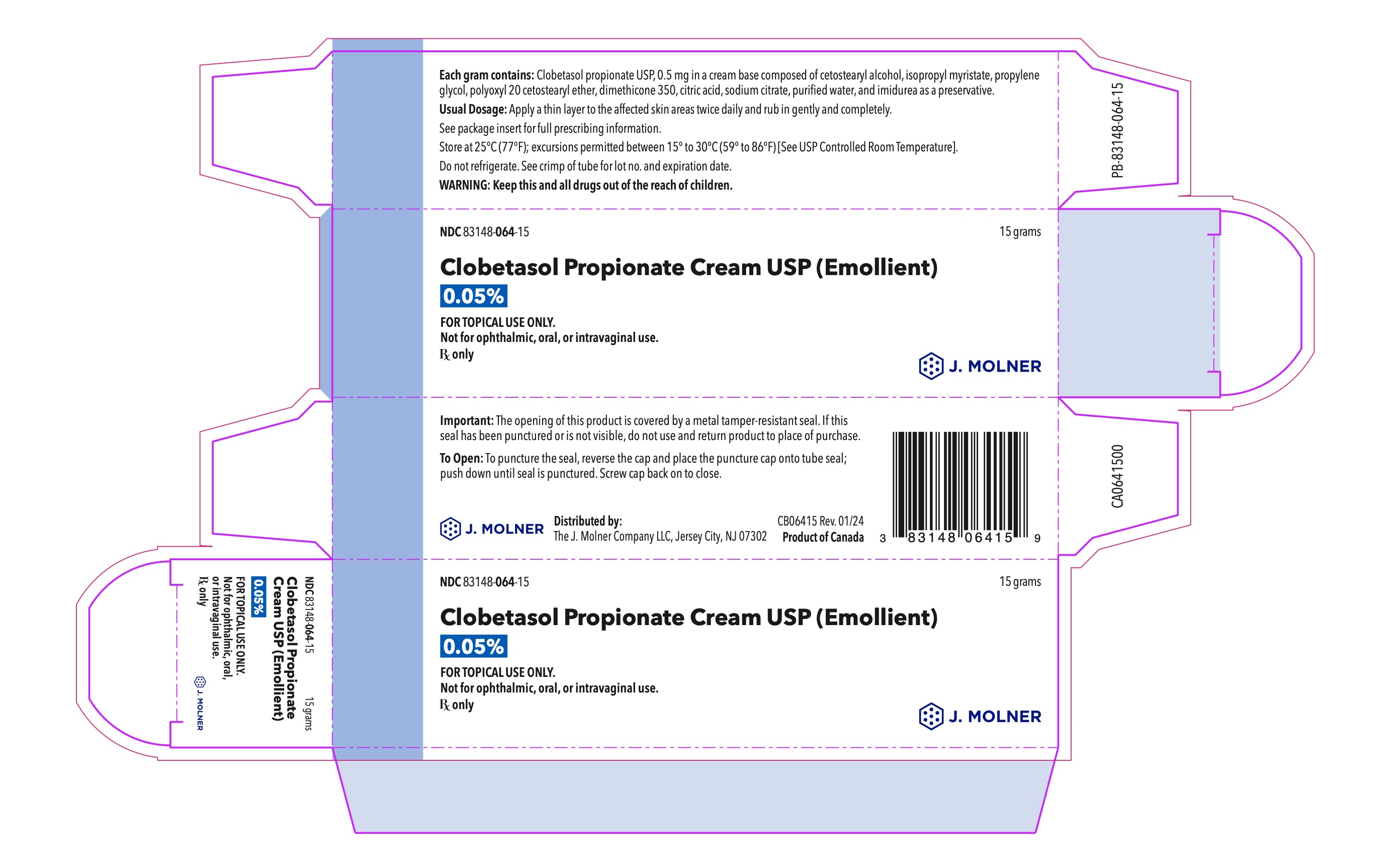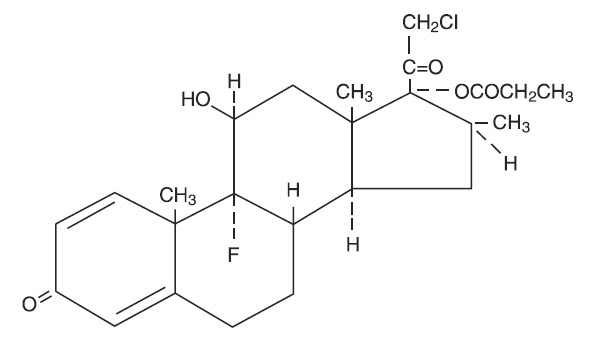 DRUG LABEL: Clobetasol Propionate (emollient)
NDC: 83148-064 | Form: CREAM
Manufacturer: The J. Molner Company LLC
Category: prescription | Type: HUMAN PRESCRIPTION DRUG LABEL
Date: 20251002

ACTIVE INGREDIENTS: CLOBETASOL PROPIONATE 0.5 mg/1 g
INACTIVE INGREDIENTS: CETOSTEARYL ALCOHOL; ISOPROPYL MYRISTATE; PROPYLENE GLYCOL; CETETH-20; DIMETHICONE 350; CITRIC ACID MONOHYDRATE; SODIUM CITRATE; WATER; IMIDUREA

HIGHLIGHTS OF PRESCRIBING INFORMATION

These highlights do not include all the information needed to use CLOBETASOL PROPIONATE CREAM (EMOLLIENT) safely and effectively. See full prescribing information for CLOBETASOL PROPIONATE CREAM (EMOLLIENT).
CLOBETASOL PROPIONATE cream, for topical use
Initial U.S. Approval: 1994

1 INDICATIONS AND USAGE

Clobetasol propionate cream USP, 0.05% (emollient) is a corticosteroid indicated for:

- The relief of the inflammatory and pruritic manifestations of corticosteroid-responsive dermatoses in patients 12 years of age or older. (1.1)
- The treatment of moderate to severe plaque-type psoriasis in patients 16 years of age and older. (1.2)

Limitations of Use

- Clobetasol propionate cream USP, 0.05% (emollient) should not be used in the treatment of rosacea or perioral dermatitis, and should not be used on the face, groin, or axillae. (1.3)
- The total dosage should not exceed 50 grams per week. (1.3)
- Avoid use if skin atrophy is present at the treatment site. (1.3)

2 DOSAGE AND ADMINISTRATION

- Apply a thin layer of Clobetasol propionate cream USP, 0.05% (emollient) to the affected skin areas twice daily and rub in gently and completely. (2)
- Treatment should be limited to 2 consecutive weeks, and amounts greater than 50 grams per week should not be used. (2)
- In moderate to severe plaque-type psoriasis, Clobetasol propionate cream USP, 0.05% (emollient) applied to 5% to 10% of body surface area can be used for up to 4 weeks. The total dosage should not exceed 50 grams per week. When dosing for more than 2 weeks, any additional benefit of extending treatment should be weighed against the risk of HPA suppression. (2)

3 DOSAGE FORMS AND STRENGTHS

Cream: 0.05% (3)

4 CONTRAINDICATIONS

None (4)

5 WARNINGS AND PRECAUTIONS

- Clobetasol propionate is a highly potent topical corticosteroid that has been shown to suppress the HPA axis doses as low as 2 grams per day. (5.1)
- Cushing's syndrome, hyperglycemia, and glucosuria can also result from systemic absorption of topical corticosteroids. (5.1)
- Systemic absorption may require periodic evaluation for HPA axis suppression. Modify use if HPA axis suppression develops. (5.1)
- Children may be more susceptible to systemic toxicity from use of topical corticosteroids. (5.1, 8.4)
- Local adverse reactions with topical corticosteroids may occur more frequently with the use of occlusive dressings and higher potency corticosteroids, including clobetasol propionate. These reactions include: folliculitis, acneiform eruptions, hypertrichosis, hypopigmentation, perioral dermatitis, allergic contact dermatitis, secondary infection, striae and miliaria. (5.2)

6 ADVERSE REACTIONS

- The most common adverse reaction is burning/stinging (incidence 5%); common adverse reactions (incidence < 2%) are pruritis, irritation, erythema, folliculitis, cracking and fissuring of the skin, numbness of the fingers, tenderness in the elbow, skin atrophy, and telangiectasia. (6.1).

To report SUSPECTED ADVERSE REACTIONS, contact The J. Molner Company LLC at 1-800-552-8750 or FDA at 1-800-FDA-1088 or www.fda.gov/medwatch.

FULL PRESCRIBING INFORMATION

1 INDICATIONS AND USAGE

Clobetasol propionate cream USP, 0.05% (emollient) is a super-high potency corticosteroid indicated for:

1.1 Corticosteroid-Responsive Dermatoses

Clobetasol propionate cream USP, 0.05% (emollient) is indicated for the relief of the inflammatory and pruritic manifestations of corticosteroid-responsive dermatoses in patients 12 years of age and older. Treatment should be limited to 2 consecutive weeks, and the total dosage should not exceed 50 grams per week.

1.2 Moderate to Severe Plaque-Type Psoriasis

Clobetasol propionate cream USP, 0.05% (emollient) is indicated for the topical treatment of moderate to severe plaque-type psoriasis. Treatment beyond 4 consecutive weeks is not recommended. Use in pediatric patients under 16 years of age is not recommended.

1.3 Limitations of Use

Clobetasol propionate cream USP, 0.05% (emollient) should not be used in the treatment of rosacea or perioral dermatitis, and should not be used on the face, groin, or axillae.

The total dosage should not exceed 50 grams per week.

Avoid use if skin atrophy is present at the treatment site.

2 DOSAGE AND ADMINISTRATION

Apply a thin layer of Clobetasol propionate cream USP, 0.05% (emollient) to the affected skin areas twice daily and rub in gently and completely. Wash hands after each application.

Clobetasol propionate cream USP, 0.05% (emollient) is a super-high potency topical corticosteroid; therefore, treatment should be limited to 2 consecutive weeks, and amounts greater than 50 grams per week should not be used.

In moderate to severe plaque-type psoriasis, Clobetasol propionate cream USP, 0.05% (emollient) applied to 5% to 10% of body surface area can be used for up to 4 weeks. The total dosage should not exceed 50 grams per week. When dosing for more than 2 weeks, any additional benefits of extending treatment should be weighed against the risk of HPA suppression. Therapy should be discontinued when control has been achieved. If no improvement is seen within 2 weeks, reassessment of diagnosis may be necessary. Treatment beyond 4 consecutive weeks is not recommended.

Clobetasol propionate cream USP, 0.05% (emollient) should not be used with occlusive dressings.

3 DOSAGE FORMS AND STRENGTHS

Cream, 0.05%. Each gram of Clobetasol propionate cream USP, 0.05% (emollient) contains 0.5 mg of clobetasol propionate in a white to off-white cream base.

4 CONTRAINDICATIONS

None

5 WARNINGS AND PRECAUTIONS

5.1 Effects on the Endocrine System

Clobetasol propionate is a highly potent topical corticosteroid that has been shown to suppress the HPA axis at doses as low as 2 grams per day.

Systemic absorption of topical corticosteroids can produce reversible HPA axis suppression with the potential for clinical glucocorticosteroid insufficiency. This may occur during treatment or upon withdrawal of the topical corticosteroid.

Because of the potential for systemic absorption, use of topical corticosteroids may require that patients be periodically evaluated for HPA axis suppression. In a study including 12 subjects ages 18 years and older with psoriasis or atopic dermatitis involving at least 30% body surface area (BSA), adrenal suppression was identified in 3 out of 12 subjects (25%) following 1 week of treatment.

Factors that predispose a patient using a topical corticosteroid to HPA axis suppression include the use of more potent steroids, use over large surface areas, use over prolonged periods, use under occlusion, use on an altered skin barrier, and use in patients with liver failure.

An ACTH stimulation test may be helpful in evaluating patients for HPA axis suppression. If HPA axis suppression is documented, an attempt should be made to gradually withdraw the drug, to reduce the frequency of application, or to substitute a less potent steroid. Manifestations of adrenal insufficiency may require supplemental systemic corticosteroids. Recovery of HPA axis function is generally prompt and complete upon discontinuation of topical corticosteroids.

Cushing's syndrome, hyperglycemia, and unmasking of latent diabetes mellitus can also result from systemic absorption of topical corticosteroids.

Use of more than one corticosteroid-containing product at the same time may increase the total systemic corticosteroid exposure.

Pediatric patients may be more susceptible to systemic toxicity from use of topical corticosteroids. [ see Use in Specific Populations (8.4)]

5.2 Local Adverse Reactions with Topical Corticosteroids

Local adverse reactions may be more likely to occur with occlusive use, prolonged use or use of higher potency corticosteroids. Reactions may include atrophy, striae, telangiectasias, burning, itching, irritation, dryness, folliculitis, acneiform eruptions, hypopigmentation, hypertrichosis, perioral dermatitis, allergic contact dermatitis, secondary infection, and miliaria. Some local adverse reactions may be irreversible. Clobetasol propionate is not recommended in patients with acne vulgaris, rosacea or perioral dermatitis.

5.3 Allergic Contact Dermatitis

Allergic contact dermatitis with corticosteroids is usually diagnosed by observing a failure to heal rather than noting a clinical exacerbation. Clinical diagnosis of allergic contact dermatitis can be confirmed with patch testing. If irritation develops, Clobetasol propionate cream, 0.05% (emollient) should be discontinued and appropriate therapy instituted.

5.4 Concomitant Skin Infections

If concomitant skin infections are present or develop, an appropriate antifungal or antibacterial agent should be used. If a favorable response does not occur promptly, use of Clobetasol propionate cream, 0.05% (emollient) should be discontinued until the infection has been adequately controlled.

6 ADVERSE REACTIONS

6.1 Clinical Trials Experience

Because clinical trials are conducted under widely varying conditions, adverse reaction rates observed in the clinical trials of a drug cannot be directly compared to rates in the clinical trials of another drug and may not reflect the rates observed in clinical practice.

In controlled trials with clobetasol propionate formulations, the following adverse reactions have been reported: burning/stinging, pruritis, irritation, erythema, folliculitis, cracking and fissuring of the skin, numbness of the fingers, tenderness in the elbow, skin atrophy, and telangiectasia. The incidence of local adverse reactions reported in the trials with Clobetasol propionate cream, 0.05% (emollient) was less than 2% of patients treated with the exception of burning/stinging which occurred in 5% of treated patients.

8 USE IN SPECIFIC POPULATIONS

8.1 Pregnancy

There are no adequate and well-controlled studies in pregnant women. Therefore, Clobetasol propionate cream, 0.05% (emollient) should be used during pregnancy only if the potential benefit justifies the potential risk to the fetus.

Corticosteroids have been shown to be teratogenic in laboratory animals when administered systemically at relatively low dosage levels. Some corticosteroids have been shown to be teratogenic after dermal application to laboratory animals.

Clobetasol propionate has not been tested for teratogenicity by this route; however, it is absorbed percutaneously, and when administered subcutaneously it was a significant teratogen in both the rabbit and mouse. Clobetasol propionate has greater teratogenic potential than steroids that are less potent.

Teratogenicity studies in mice using the subcutaneous route resulted in fetotoxicity at the highest dose tested (1 mg/kg) and teratogenicity at all dose levels tested down to 0.03 mg/kg. These doses are approximately 0.33 and 0.01 times, respectively, the human topical dose of Clobetasol propionate cream, 0.05% (emollient). Abnormalities seen included cleft palate and skeletal abnormalities.

In rabbits, clobetasol propionate was teratogenic at doses of 3 and 10 mcg/kg. These doses are approximately 0.001 and 0.003 times, respectively, the human topical dose of Clobetasol propionate cream, 0.05% (emollient). Abnormalities seen included cleft palate, cranioschisis, and other skeletal abnormalities.

8.2 Lactation

Systemically administered corticosteroids appear in human milk and could suppress growth, interfere with endogenous corticosteroid production, or cause other untoward effects. It is not known whether topical administration of corticosteroids could result in sufficient systemic absorption to produce detectable quantities in human milk. Because many drugs are excreted in human milk, caution should be exercised when Clobetasol propionate cream, 0.05% (emollient) is administered to a nursing woman.

8.4 Pediatric Use

Safety and effectiveness of Clobetasol propionate cream, 0.05% (emollient) in pediatric patients have not been established and its use in pediatric patients under 12 years of age is not recommended. In a study including 12 subjects ages 18 years and older with psoriasis or atopic dermatitis involving at least 30% body surface area (BSA), adrenal suppression was identified in 3 out of 12 subjects (25%) following 1 week of treatment. Four-week HPA axis suppression studies with Clobetasol propionate cream, 0.05% (emollient) in pediatric subjects have not been conducted.

Because of a higher ratio of skin surface area to body mass, pediatric patients are at a greater risk than adults of HPA axis suppression and Cushing's syndrome when they are treated with topical corticosteroids. They are therefore also at greater risk of glucocorticosteroid insufficiency during or after withdrawal of treatment. Adverse effects including striae have been reported with inappropriate use of topical corticosteroids in infants and children.

HPA axis suppression, Cushing's syndrome, linear growth retardation, delayed weight gain, and intracranial hypertension have been reported in children receiving topical corticosteroids. Manifestations of adrenal suppression in children include low plasma cortisol levels and absence of response to ACTH stimulation. Manifestations of intracranial hypertension include bulging fontanelles, headaches, and bilateral papilledema.

The use of Clobetasol propionate cream, 0.05% (emollient) for 4 consecutive weeks has not been studied in pediatric patients under 16 years of age.

8.5 Geriatric Use

Clinical studies of Clobetasol propionate cream, 0.05% (emollient) did not include sufficient numbers of subjects aged 65 and older to determine whether they respond differently from younger subjects. In general, dose selection for an elderly patient should be cautious.

10 OVERDOSAGE

Topically applied Clobetasol propionate cream, 0.05% (emollient) can be absorbed in sufficient amounts to produce systemic effects [ see Warnings and Precautions (5.1)].

11 DESCRIPTION

Clobetasol propionate cream USP, 0.05% (emollient) contains the active compound clobetasol propionate, a synthetic corticosteroid, for topical use. Clobetasol, an analog of prednisolone, has a high degree of glucocorticoid activity and a slight degree of mineralocorticoid activity.

Chemically, clobetasol propionate is (11β,16β)-21-chloro-9-fluoro-11-hydroxy-16-methyl-17-(1-oxopropoxy)-pregna-1,4-diene-3,20-dione, and it has the following structural formula:

Clobetasol propionate has the molecular formula C25H32ClFO5 and a molecular weight of 467. It is a white to cream-colored crystalline powder insoluble in water.

Each gram of Clobetasol propionate cream USP, 0.05% (emollient) contains 0.5 mg of clobetasol propionate in a white to off-white cream base consisting of cetostearyl alcohol, isopropyl myristate, propylene glycol, polyoxyl 20 cetostearyl ether, dimethicone 350, citric acid, sodium citrate, purified water, and imidurea as a preservative.

12 CLINICAL PHARMACOLOGY

12.1 Mechanism of Action

Like other topical corticosteroids, clobetasol propionate has anti-inflammatory, antipruritic, and vasoconstrictive properties. The mechanism of the anti-inflammatory activity of the topical steroids, in general, is unclear. However, corticosteroids are thought to act by the induction of phospholipase A2 inhibitory proteins, collectively called lipocortins. It is postulated that these proteins control the biosynthesis of potent mediators of inflammation such as prostaglandins and leukotrienes by inhibiting the release of their common precursor, arachidonic acid. Arachidonic acid is released from membrane phospholipids by phospholipase A2.

12.2 Pharmacodynamics

Clobetasol propionate cream, 0.05% (emollient) is in the super-high range of potency as demonstrated in a vasoconstrictor study in healthy subjects when compared with other topical corticosteroids. However, similar blanching scores do not necessarily imply therapeutic equivalence.

12.3 Pharmacokinetics

The extent of percutaneous absorption of topical corticosteroids is determined by many factors, including the vehicle and the integrity of the epidermal barrier. Topical corticosteroids can be absorbed from normal intact skin. Inflammation and/or other disease processes in the skin may increase percutaneous absorption.

13 NONCLINICAL TOXICOLOGY

13.1 Carcinogenesis, Mutagenesis, Impairment of Fertility

Carcinogenesis
Long-term animal studies have not been performed to evaluate the carcinogenic potential of clobetasol propionate.

Mutagenesis
Clobetasol propionate was nonmutagenic in three different test systems: the Ames test, the Saccharomyces cerevisiae gene conversion assay, and the E. Coli B WP2 fluctuation test.

Impairment of Fertility
Studies in the rat following oral administration at dosage levels up to 50 mg/kg per day revealed no significant effect on the males. The females exhibited an increase in the number of resorbed embryos and a decrease in the number of living fetuses at the highest dose.

14 CLINICAL STUDIES

In a controlled clinical trial involving patients with moderate to severe plaque-type psoriasis, Clobetasol propionate cream, 0.05% (emollient) was applied to 5% to 10% of body surface area. In this trial, there were no clobetasol-treated patients with clinically significant decreases in morning cortisol levels after 4 weeks of treatment; however, morning cortisol levels may not identify patients with adrenal dysfunction.

16 HOW SUPPLIED/STORAGE AND HANDLING

How Supplied
Clobetasol Propionate Cream USP, 0.05% (emollient), is a white to off-white cream, supplied as follows:
NDC 83148-064-15 15 g tube
NDC 83148-064-30 30 g tube
NDC 83148-064-60 60 g tube

Storage and Handling

Store at 25°C (77°F); excursions permitted between 15° to 30°C (59° to 86°F) [See USP Controlled Room Temperature].

Clobetasol Propionate Cream USP, 0.05% (emollient) should not be refrigerated.

17 PATIENT COUNSELING INFORMATION

Inform patients using topical corticosteroids of the following information and instructions:

- Clobetasol propionate cream USP, 0.05% (emollient) is for external use only. Avoid contact with the eyes.
- Use as directed. Do not use Clobetasol propionate cream USP, 0.05% (emollient) for any disorder other than that for which it was prescribed. Do not use longer than the prescribed time period.
- Do not use other corticosteroid-containing products while using Clobetasol propionate cream USP, 0.05% (emollient) unless directed by the physician.
- The treated skin area should not be bandaged, otherwise covered, or wrapped so as to be occlusive unless directed by the physician.
- Wash hands after applying the medication.
- Report any signs of local or systemic adverse reactions to the physician.
- Inform their physicians that they are using Clobetasol propionate cream USP, 0.05% (emollient) if surgery is contemplated. If you go to another doctor for illness, injury or surgery, tell the doctor you are using Clobetasol propionate cream USP, 0.05% (emollient).
- Do not use Clobetasol propionate cream USP, 0.05% (emollient) on the face, underarms or groin areas.
- As with other corticosteroids, therapy should be discontinued when control is achieved. If no improvement is seen within 2 weeks, contact the physician.
- Use no more than 50 grams per week of Clobetasol propionate cream USP, 0.05% (emollient).
- Store between 59°F and 86°F (15°C and 30°C). Do not refrigerate.

Distributed by:
The J. Molner Company LLC,

Jersey City, NJ 07302

Product of Canada

Rev. 02/2024

PI064

Package Label - Principal Display Panel – 15g Tube Carton

NDC 83148-064-15

Clobetasol Propionate Cream USP, 0.05% (Emollient)

FOR TOPICAL USE ONLY.
Not for ophthalmic, oral, or intravaginal use.

15 grams
Rx only